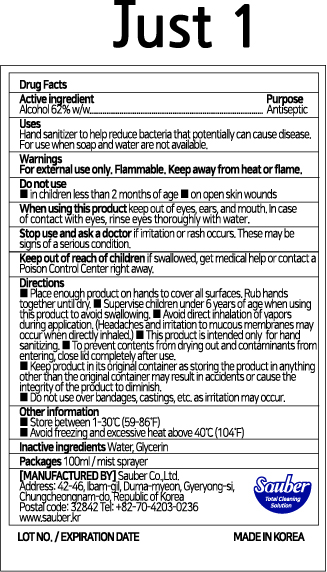 DRUG LABEL: Just 1
NDC: 78880-162 | Form: SPRAY
Manufacturer: Sauber Co.,Ltd.
Category: otc | Type: HUMAN OTC DRUG LABEL
Date: 20200629

ACTIVE INGREDIENTS: ALCOHOL 62 mL/100 mL
INACTIVE INGREDIENTS: GLYCERIN; WATER

Just 1 | 100 ml | Mist sprayer